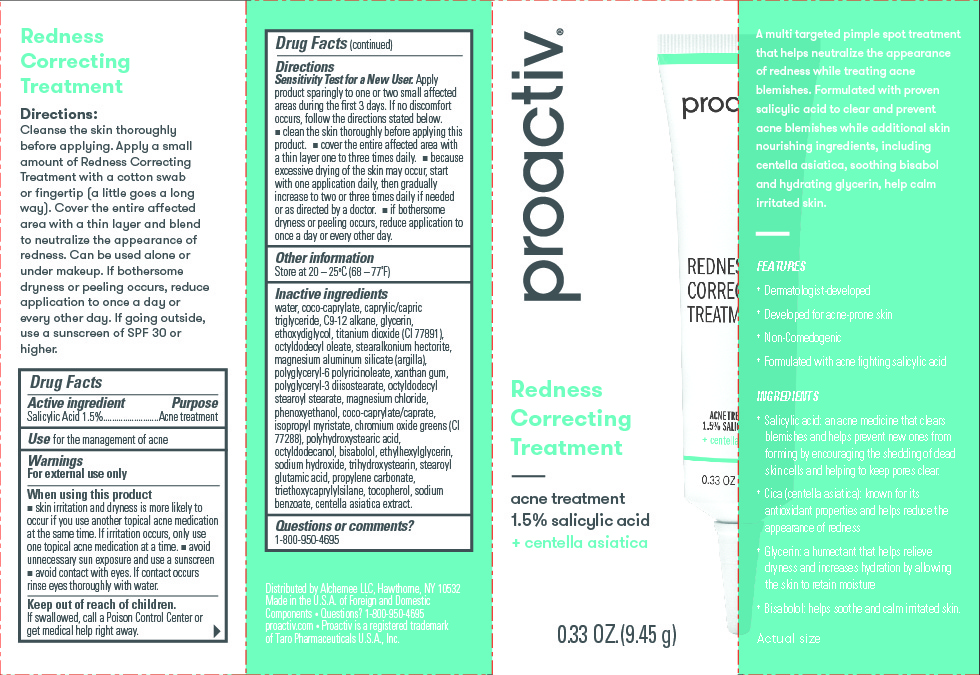 DRUG LABEL: Proactiv Redness Correcting Treatment
NDC: 11410-219 | Form: CREAM
Manufacturer: Alchemee, LLC
Category: otc | Type: HUMAN OTC DRUG LABEL
Date: 20260107

ACTIVE INGREDIENTS: SALICYLIC ACID 1.5 g/100 mL
INACTIVE INGREDIENTS: ETHYLHEXYLGLYCERIN; TRIETHOXYCAPRYLYLSILANE; SODIUM BENZOATE; TITANIUM DIOXIDE; BISABOLOL; MAGNESIUM ALUMINUM SILICATE; PROPYLENE CARBONATE; C9-12 ALKANE; GLYCERIN; COCO-CAPRYLATE/CAPRATE; STEARALKONIUM HECTORITE; WATER; ETHOXYDIGLYCOL; CAPRYLIC/CAPRIC TRIGLYCERIDE; OCTYLDODECYL STEAROYL STEARATE; PHENOXYETHANOL; STEAROYL GLUTAMIC ACID; CENTELLA ASIATICA TRITERPENOIDS; OCTYLDODECYL OLEATE; POLYGLYCERYL-6 POLYRICINOLEATE; XANTHAN GUM; POLYGLYCERYL-3 DIISOSTEARATE; CHROMIUM OXIDE GREENS; SODIUM HYDROXIDE; POLYHYDROXYSTEARIC ACID STEARATE; ISOPROPYL MYRISTATE; OCTYLDODECANOL; TRIHYDROXYSTEARIN; TOCOPHEROL; COCO-CAPRYLATE; MAGNESIUM CHLORIDE

Proactiv Redness Correcting Treatment

Drug Facts

Active Ingredient

Salicylic acid 1.5%

Purpose

Acne Treatment

Use

for the management of acne

Warnings

For external use only

When Using this Product

- skin irritation and dryness is more likely to occur if you use another topical acne medication at the same time. If irritation occurs, only use one topical acne medication at a time.
- avoid unnecessary sun exposure and use a sunscreen
- avoid contact with eyes. If contact occurs, rinse eyes thoroughly with water.

Keep out of reach of children

If swallowed, get medical help or contact a Poison Control Center right away.

Directions

- Sensitivity Test for a New User. Apply product sparingly to one or two small affected areas during the first 3 days. If no discomfort occurs, follow the directions stated below.
- clean the skin thoroughly before applying this product
- cover the entire affected area with a thin layer one to three times daily
- because excessive drying of the skin may occur, start with one application daily, then gradually increase to two or three times daily if needed or as directed by a doctor
- if bothersome dryness or peeling occurs, reduce application to once a day or every other day.

Other Information

Store at 20 - 25°C (68 - 77°F)

Inactive ingredients

Water, Coco-Caprylate, Caprylic/Capric Triglyceride, C9-12 Alkane, Glycerin, Ethoxydiglycol, Titanium Dioxide (CI 77891), Octyldodecyl Oleate, Stearalkonium Hectorite, Magnesium Aluminum Silicate (Argilla), Polyglyceryl-6 Polyricinoleate, Xanthan Gum, Polyglyceryl-3 Diisostearate, Octyldodecyl Stearoyl Stearate, Magnesium Chloride, Phenoxyethanol, Coco-Caprylate/Caprate, Isopropyl Myristate, Chromium Oxide Greens (CI 77288), Polyhydroxystearic Acid, Octyldodecanol, Bisabolol, Ethylhexylglycerin, Sodium Hydroxide, Trihydroxystearin, Stearoyl Glutamic Acid, Propylene Carbonate, Triethoxycaprylylsilane, Tocopherol, Sodium Benzoate, Centella Asiatica Extract.

Questions or comments?

1-800-950-4695

PRINCIPAL DISPLAY PANEL - 89 mL

proactiv

Redness

Correcting

Treatment

acne treatment

1.5% salicylic acid

+ centella asiatica

0.33 OZ. (9.45 g)